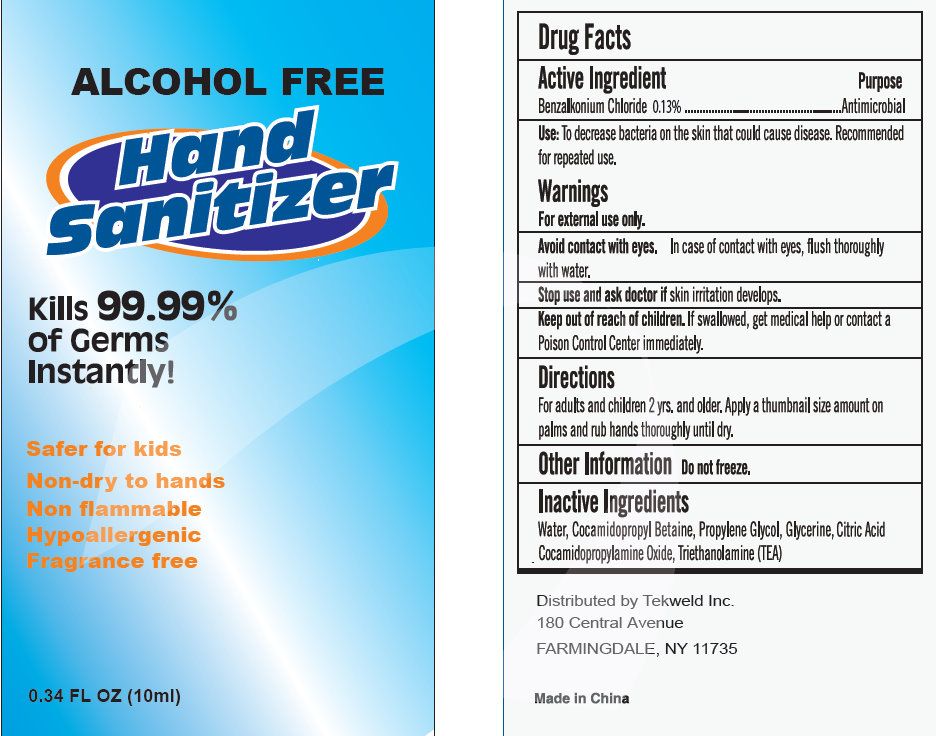 DRUG LABEL: ALCOHOL FREE HAND SANITIZER
NDC: 31190-800 | Form: GEL
Manufacturer: Shanghai Kejing Cleaning Products Co., Ltd.
Category: otc | Type: HUMAN OTC DRUG LABEL
Date: 20110912

ACTIVE INGREDIENTS: BENZALKONIUM CHLORIDE .13 mL/100 mL
INACTIVE INGREDIENTS: WATER; COCAMIDOPROPYL BETAINE; PROPYLENE GLYCOL; GLYCERIN; COCAMIDOPROPYLAMINE OXIDE; TROLAMINE

ALCOHOL FREE HAND SANITIZER

Active Ingredient
Benzalkonium Chloride 0.13percent.

Purpose

Antimicrobial

INDICATIONS AND USAGE

Use: To decrease bacterial on the skin that could cause disease. Recommended for repeated use.

Warnings

For external use only.

Avoid contact with eyes. In case of contact with eyes, flush thoroughly with water.

Stop use and ask doctor if skin irritation develops.

Keep out of reach of children. If swallowed, get medical help or contact a Poison Control Center immediately.

Directions
For adults and children 2 yrs. and older. Apply a thumbnail size amount on palms and rub hands thoroughly until dry.

Other Information:

Do not freeze

INACTIVE INGREDIENT

Inactive Ingredients: Water, Cocamidopropyl Betaine, Propylene Glycol, Glycerine, Citric Acid,
Cocamidopropylamine Oxide, Triethanolamine (TEA)

DESCRIPTION

Distributed by Tekweld Inc.
180 Central Avenue
FARMINGDALE, NY 11735
Made in China

PACKAGE LABEL

Alcohol Free

Hand Sanitizer

Kills 99.99percent

of Germs

Instantly

Safe for kids

Non-dry to hands

Non flammable

Hypoallergenic

Fragrance free

0.34 FL OZ (10ml)